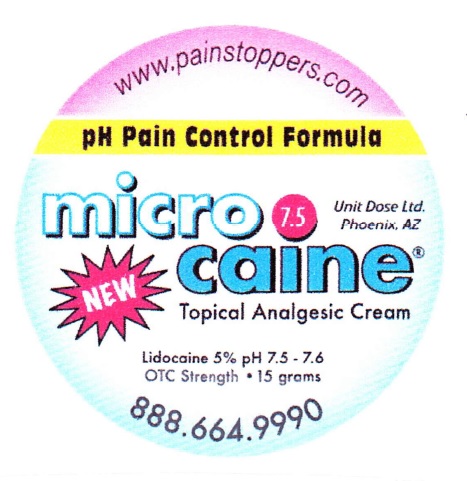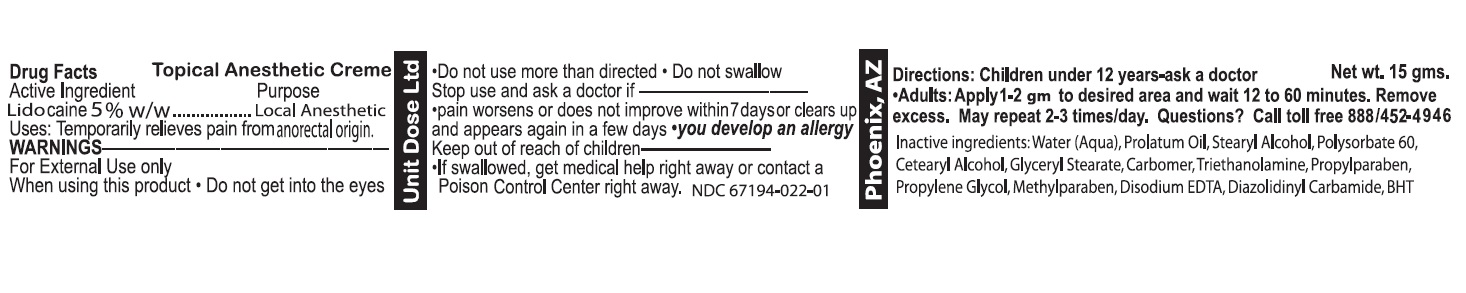 DRUG LABEL: Microcaine Topical Analgesic
NDC: 67194-022 | Form: CREAM
Manufacturer: Unit Dose, Ltd.
Category: otc | Type: HUMAN OTC DRUG LABEL
Date: 20231019

ACTIVE INGREDIENTS: LIDOCAINE 50 mg/1 g
INACTIVE INGREDIENTS: WATER; STEARYL ALCOHOL; POLYSORBATE 60; CETOSTEARYL ALCOHOL; GLYCERYL MONOSTEARATE; TROLAMINE; PROPYLPARABEN; PROPYLENE GLYCOL; METHYLPARABEN; EDETATE DISODIUM; BUTYLATED HYDROXYTOLUENE

Microcaine Topical Analgesic Cream

Active Ingredient

Lidocaine 5% w/w

Purpose

Local Anesthetic

Uses:

Temporarily relieves pain from anorectal origin.

WARNINGS

For External Use only

When using this product

- Do not get into the eyes
- Do not use more than directed
- Do not swallow

Stop use and ask a doctor if

- pain worsens or does not improve within 7 days or clears up and appears again in a few days
- you develop an allergy

Keep out of reach of children

- If swallowed, get medical help right away or contact a Poison Control Center right away. NDC 67194-022-01

Directions:

Children under 12 years-ask a doctor

- Adults: Apply 1-2 gm to desired area and wait 12 to 60 minutes. Remove excess. May repeat 2-3 times/day.

Questions?

Call toll free 888/452-4946

Inactive ingredients:

Water (Aqua), Prolatum Oil. Stearyl Alcohol, Polysorbate 60, Cetearyl Alcohol, Glyceryl Stearate, Carbomer, Triethanolamine, Propylparaben, Propylene Glycol, Methylparaben, Disodium EDTA, Diazolidinyl Carbamide, BHT